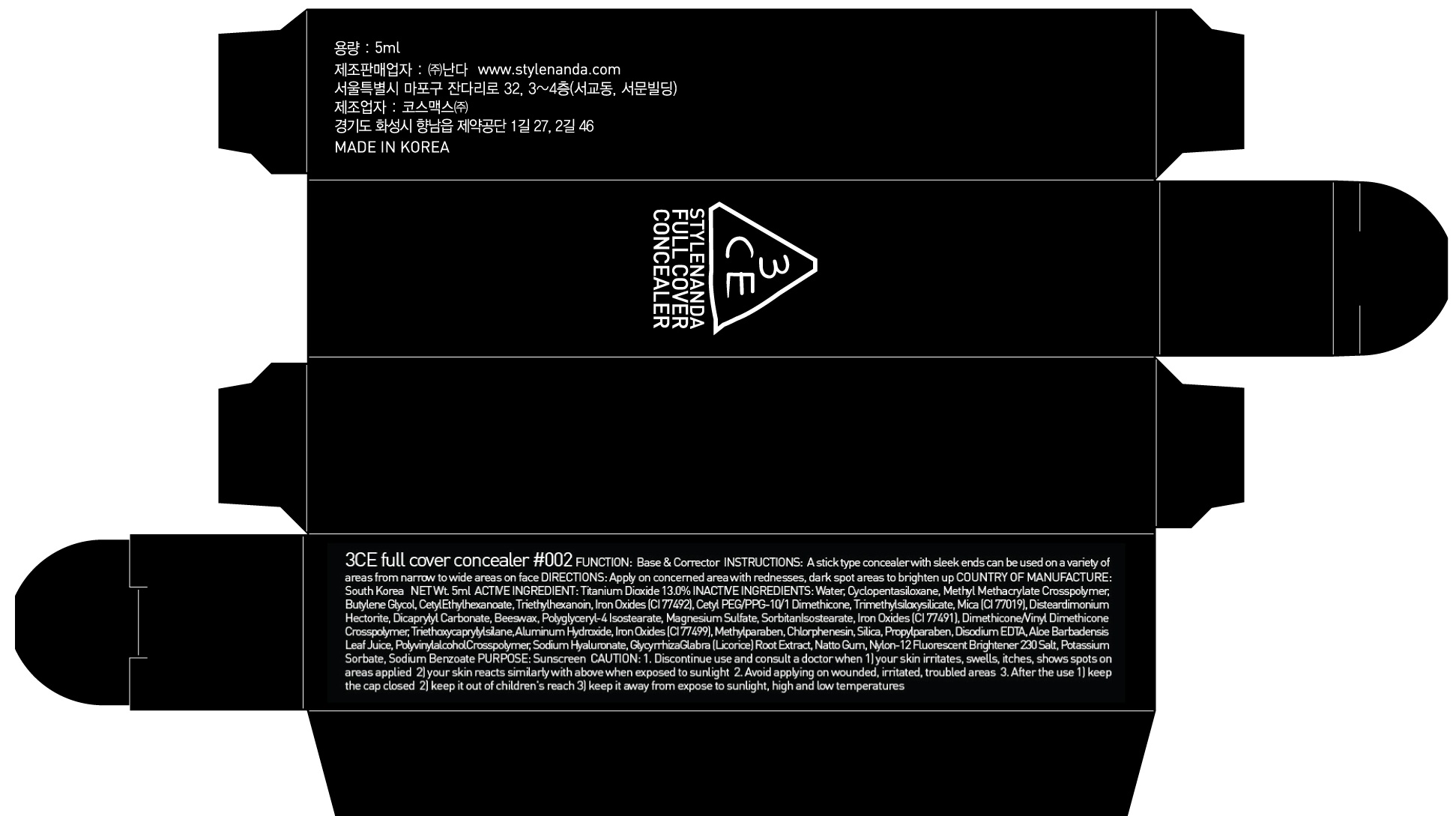 DRUG LABEL: 3CE FULL COVER CONCEALER 002
NDC: 60764-099 | Form: LIQUID
Manufacturer: Nanda Co., Ltd
Category: otc | Type: HUMAN OTC DRUG LABEL
Date: 20161012

ACTIVE INGREDIENTS: Titanium Dioxide 0.65 g/5 mL
INACTIVE INGREDIENTS: Water; Butylene Glycol

ACTIVE INGREDIENT

Active Ingredient: Titanium Dioxide 13.0%

INACTIVE INGREDIENT

Inactive Ingredients: Water, Cyclopentasiloxane, Methyl Methacrylate Crosspolymer, Butylene Glycol, CetylEthylhexanoate, Triethylhexanoin, Iron Oxides (CI 77492), Cetyl PEG/PPG-10/1 Dimethicone, Trimethylsiloxysilicate, Mica (CI 77019), DisteardimoniumHectorite, Dicaprylyl Carbonate, Beeswax, Polyglyceryl-4 Isostearate, Magnesium Sulfate, SorbitanIsostearate, Iron Oxides (CI 77491), Dimethicone/Vinyl DimethiconeCrosspolymer, Triethoxycaprylylsilane, Aluminum Hydroxide, Iron Oxides (CI 77499), Methylparaben, Chlorphenesin, Silica, Propylparaben, Disodium EDTA, Aloe Barbadensis Leaf Juice, PolyvinylalcoholCrosspolymer, Sodium Hyaluronate, GlycyrrhizaGlabra (Licorice) Root Extract, Natto Gum, Nylon-12 Fluorescent Brightener 230 Salt, Potassium Sorbate, Sodium Benzoate

PURPOSE

Purpose: Sunscreen

CAUTION

CAUTION: 1. Discontinue use and consult a doctor when - your skin irritates, swells, itches, shows spots on areas applied - your skin reacts similarly with above when exposed to sunlight 2. Avoid applying on wounded, irritated, troubled areas 3. After the use - keep the cap closed - keep it out of children's reach - keep it away from expose to sunlight, high and low temperatures

DESCRIPTION

INSTRUCTIONS: A stick type concealer with sleek ends can be used on a variety of areas from narrow to wide areas on face.

Directions: Apply on concerned area with rednesses, dark spot areas to brighten up.